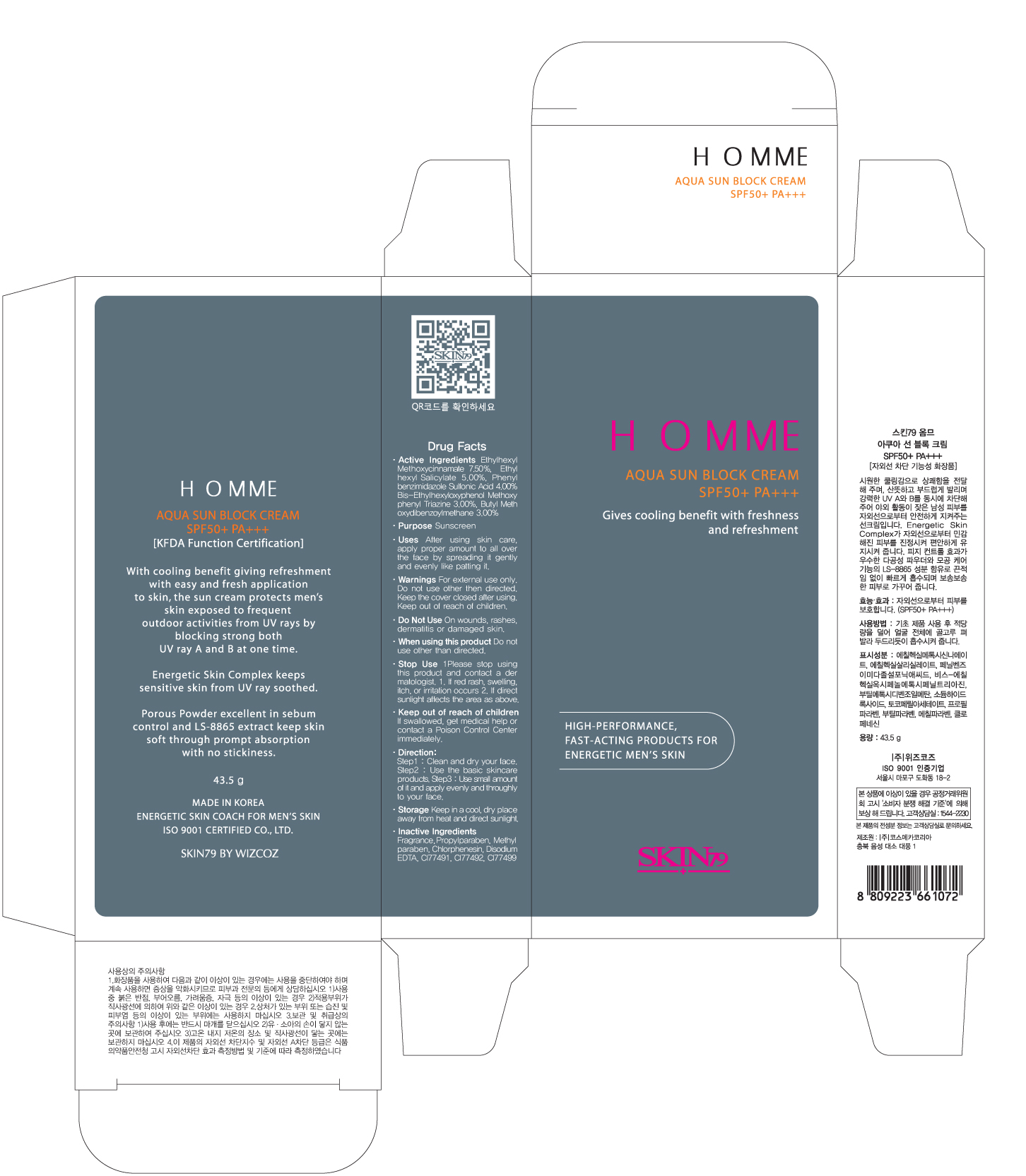 DRUG LABEL: Homme Aqua Sun Block SPF50 Plus PA 2Plus
NDC: 49715-013 | Form: CREAM
Manufacturer: WIZCOZ CORPORATION LTD
Category: otc | Type: HUMAN OTC DRUG LABEL
Date: 20111201

ACTIVE INGREDIENTS: OCTINOXATE 3.26 g/43.5 g; OCTISALATE 2.175 g/43.5 g; ENSULIZOLE 1.74 g/43.5 g; BEMOTRIZINOL 1.305 g/43.5 g; AVOBENZONE 1.305 g/43.5 g
INACTIVE INGREDIENTS: CHLORPHENESIN; EDETATE DISODIUM; METHYLPARABEN; PROPYLPARABEN

Purpose: Sunscreen

ACTIVE INGREDIENT

Active Ingredients: Octinoxate 7.50%, Octisalate 5.00%, Ensulizole 4.00%, Bemotrizinol 3.00%, Avobenzone 3.00%

When using this product: Do not use other than directed

Do Not Use: On wounds, rashes, dermatitis or damaged skin

Keep Out of Reach of Children: If swallowed, get medical help or contact a Poison Control Center immediately

Stop Use: Please stop using this product and contact a dermatologist.
1. If red rash, swelling, itch or irritation occurs
2. If direct sunlight affects the area as above

WARNINGS

Warnings: For external use only. Do not use other than directed. Keep the lid back on after using

STORAGE AND HANDLING

Storage: Keep in a cool, dry place away from heat and direct sunlight

DESCRIPTION

Direction:
Step 1: Clean and dry your face
Step 2: Use the basic skincare products
Step 3: Use small amount of it and apply evenly and thoroughly to your face

INACTIVE INGREDIENT

Inactive Ingredients: Chlorphenesin, Edetate Disodium, Methylparaben, Propylparaben